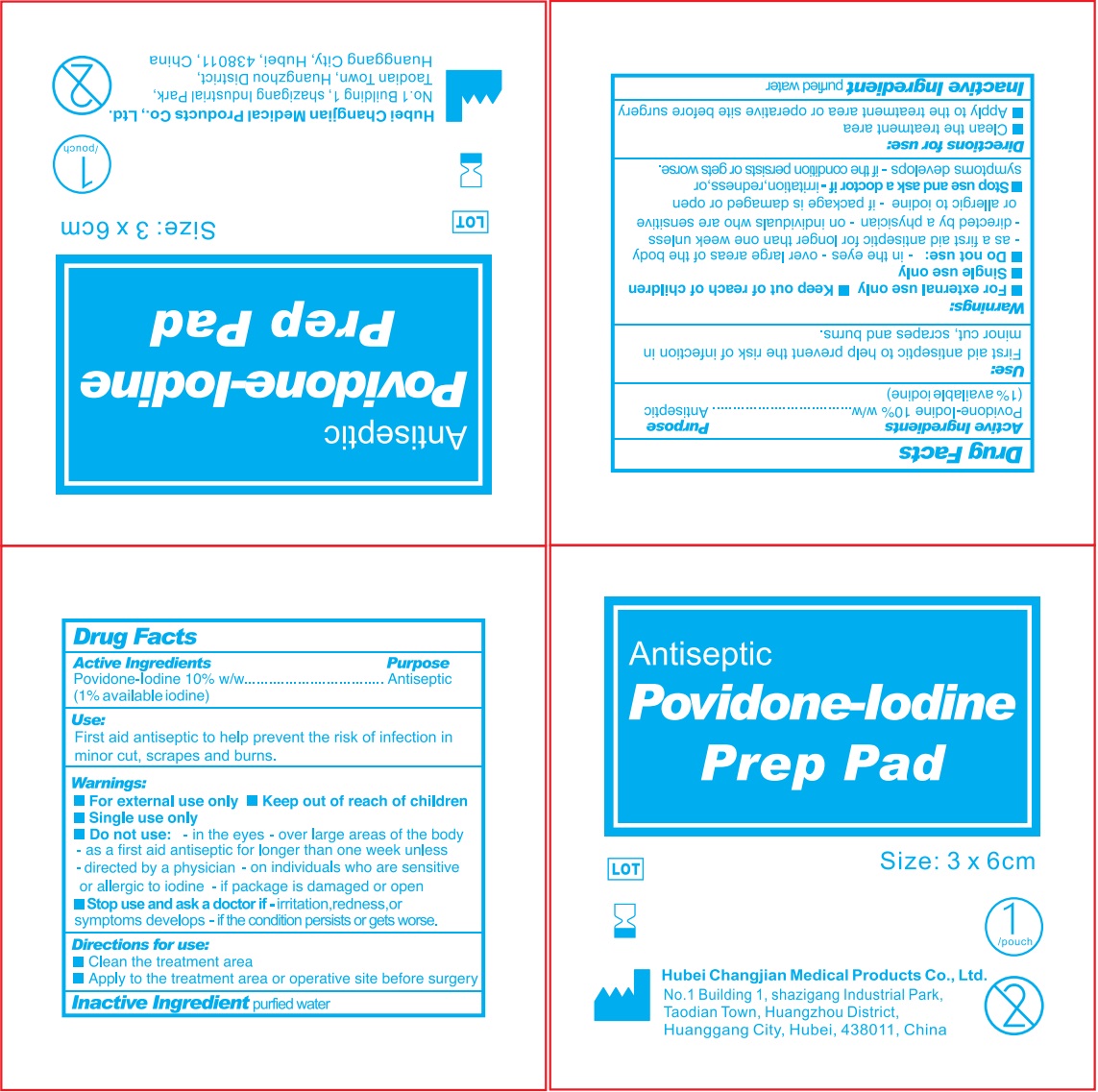 DRUG LABEL: Antiseptic Povidone-lodine Prep Pad
NDC: 82996-006 | Form: CLOTH
Manufacturer: Hubei Changjian Medical Products Co., Ltd.
Category: otc | Type: HUMAN OTC DRUG LABEL
Date: 20241011

ACTIVE INGREDIENTS: POVIDONE-IODINE 10 mg/1 g
INACTIVE INGREDIENTS: GLYCERYL MONOSTEARATE; GLYCERIN; WATER

Antiseptic Povidone-lodine Prep Pad

Active ingredients

Povidone-Iodine 10% w/w

(1% available iodine)

Purpose

First aid antiseptic

Pain relieving cream

Uses

- First aid antiseptic to help prevent the risk of infection in minor cut, scrapes, and burns.

Warnings:

- For external use only
- Keep out of reach of children
- Single use only

Do not use:

- in the eyes
- over large areas of the body
- as a first aid antiseptic for longer than one week unless directed by a physician
- on individuals who are sensitive or allergic to iodine
- if package is damaged or open

Stop use and ask a doctor if

- irritation, redness, or symptoms develops
- if the condition persists or gets worse.

Directions for use:

- Clean the treatment area
- Apply to the treatment area or operative site before surgery

Inactive ingredients

purified water